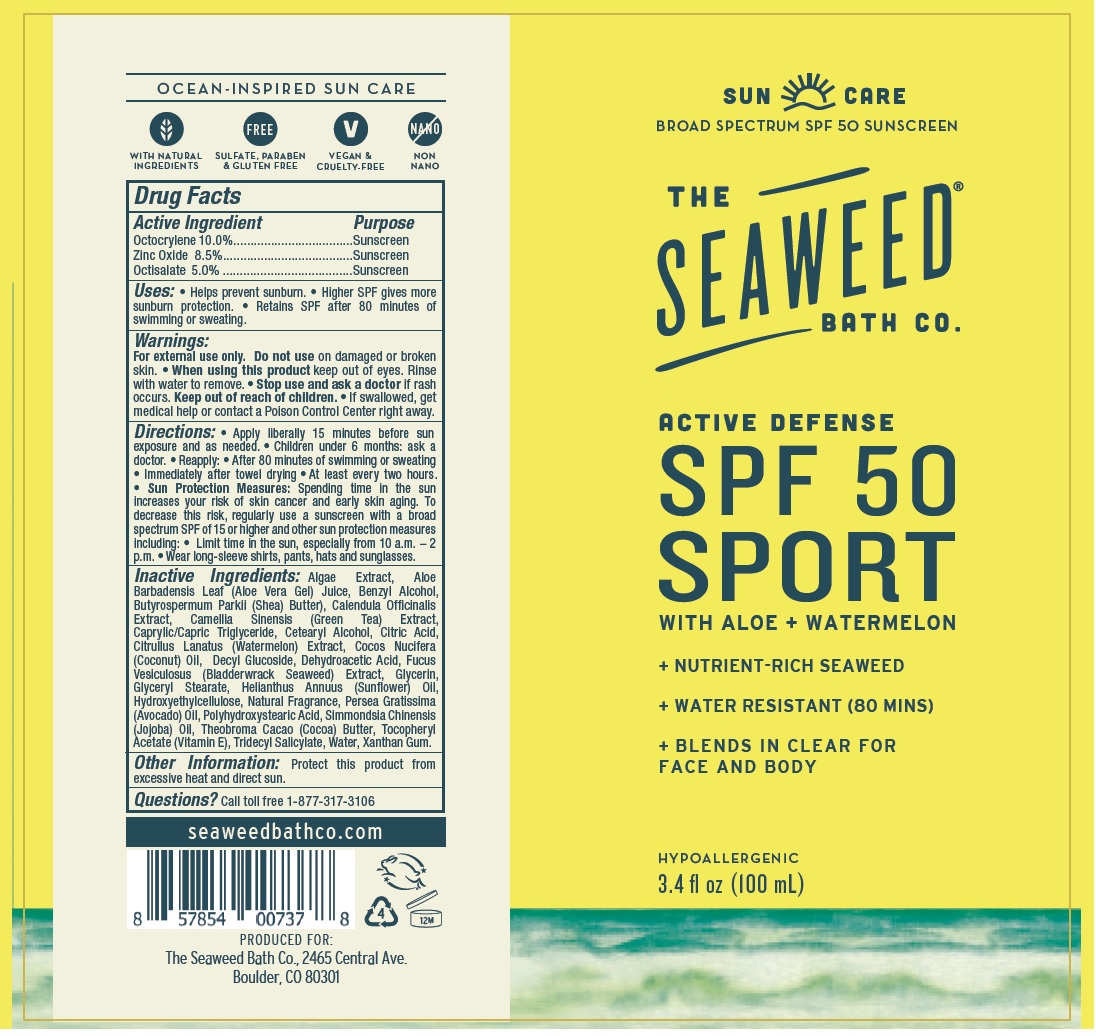 DRUG LABEL: SEAWEED BATH CO. SPF 50 SPORT
NDC: 81159-131 | Form: LOTION
Manufacturer: The Seaweed Bath Co.
Category: otc | Type: HUMAN OTC DRUG LABEL
Date: 20231111

ACTIVE INGREDIENTS: OCTOCRYLENE 100 mg/1 mL; ZINC OXIDE 85 mg/1 mL; OCTISALATE 50 mg/1 mL
INACTIVE INGREDIENTS: ALOE VERA LEAF; BENZYL ALCOHOL; SHEA BUTTER; CALENDULA OFFICINALIS FLOWER; GREEN TEA LEAF; MEDIUM-CHAIN TRIGLYCERIDES; CETOSTEARYL ALCOHOL; CITRIC ACID MONOHYDRATE; WATERMELON; COCONUT OIL; DECYL GLUCOSIDE; DEHYDROACETIC ACID; FUCUS VESICULOSUS; GLYCERIN; GLYCERYL MONOSTEARATE; HELIANTHUS ANNUUS FLOWERING TOP; HYDROXYETHYL CELLULOSE, UNSPECIFIED; AVOCADO OIL; JOJOBA OIL; COCOA; .ALPHA.-TOCOPHEROL ACETATE; TRIDECYL SALICYLATE; WATER; XANTHAN GUM

SEAWEED BATH CO. SPF-50 SPORT LOTION

Active Ingredient

Octocrylene 10.0%

Zinc Oxide 8.5%

Octisalate 5.0%

Purpose

Sunscreen

Uses:

• Helps prevent sunburn. • Higher SPF gives more sunburn protection. • Retains SPF after 80 minutes of swimming or sweating.

Warnings:

For external use only.

Do not use

on damaged or broken skin.

When using this product

- keep out of eyes. Rinse with water to remove.

Stop use and ask a doctor

- if rash occurs.

Keep out of reach of children.

• If swallowed, get medical help or contact a Poison Control Center right away.

Directions:

• Apply liberally 15 minutes before sun exposure and as needed. • Children under 6 months: ask a doctor. • Reapply: • After 80 minutes of swimming or sweating • Immediately after towel drying • A t least every two hours. • Spending time in the sun increases your risk of skin cancer and early skin aging. To decrease this risk, regularly use a sunscreen with a broad spectrum SPF of 15 or higher and other sun protection measures including: • Limit time in the sun, especially from 10 a.m. – 2 p.m. • Wear long-sleeve shirts, pants, hats and sunglasses. Sun Protection Measures:

Inactive Ingredients:

Algae Extract, Aloe Barbadensis Leaf (Aloe Vera Gel) Juice, Benzyl Alcohol, Butyrospermum Parkii (Shea) Butter), Calendula Officinalis Extract, Camellia Sinensis (Green Tea) Extract, Caprylic/Capric Triglyceride, Cetearyl Alcohol, Citric Acid, Citrullus Lanatus (Watermelon) Extract, Cocos Nucifera (Coconut) Oil, Decyl Glucoside, Dehydroacetic Acid, Fucus Vesiculosus (Bladderwrack Seaweed) Extract, Glycerin, Glyceryl Stearate, Helianthus Annuus (Sunflower) Oil, Hydroxyethylcellulose, Natural Fragrance, Persea Gratissima (Avocado) Oil, Polyhydroxystearic Acid, Simmondsia Chinensis (Jojoba) Oil, Theobroma Cacao (Cocoa) Butter, Tocopheryl Acetate (Vitamin E), Tridecyl Salicylate, Water, Xanthan Gum.

Other Information:

Protect this product from excessive heat and direct sun.

Questions?

Call toll free 1-877-317-3106